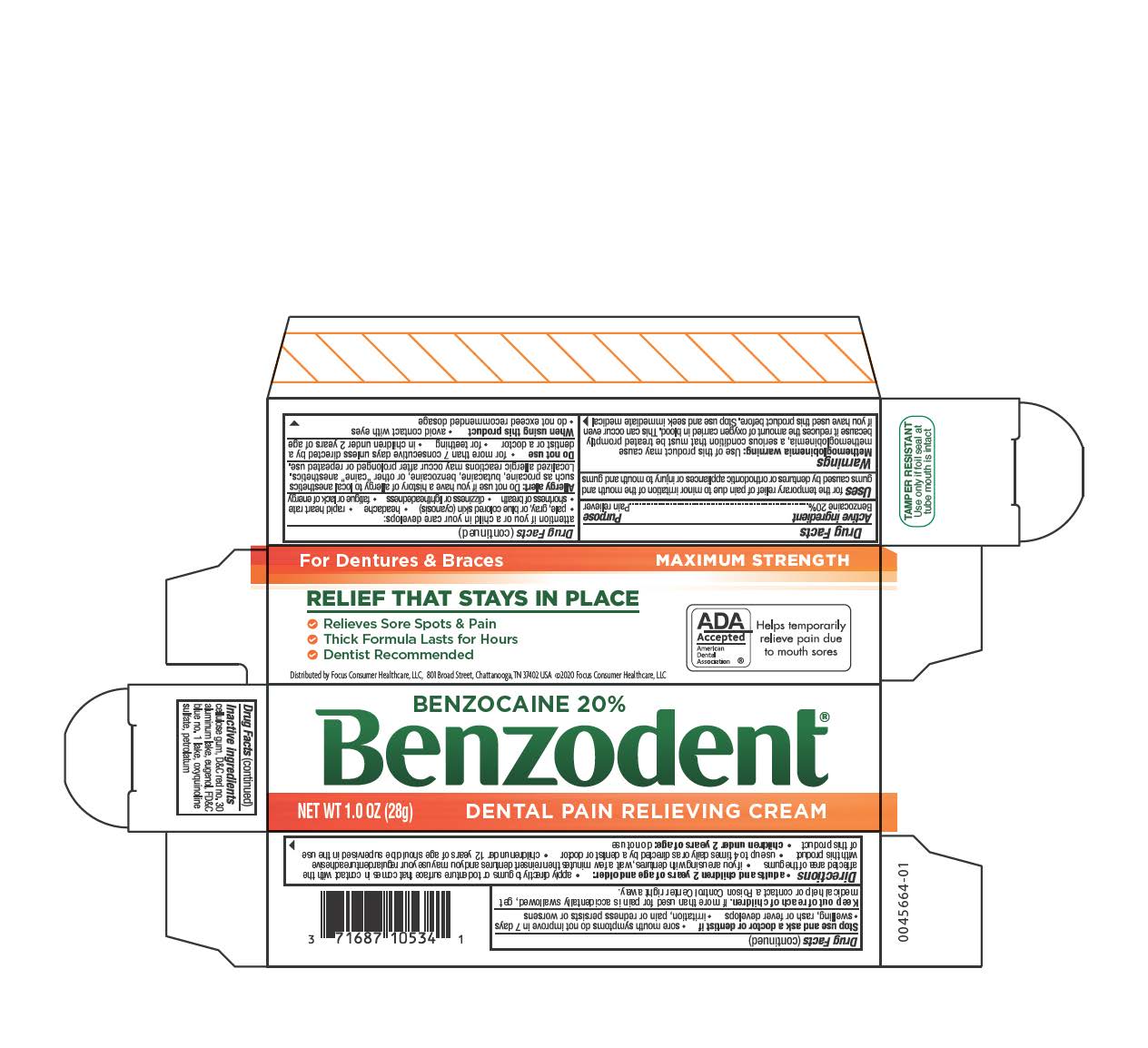 DRUG LABEL: Benzodent
NDC: 71687-1053 | Form: CREAM
Manufacturer: Focus Consumer Healthcare, LLC
Category: otc | Type: HUMAN OTC DRUG LABEL
Date: 20250414

ACTIVE INGREDIENTS: BENZOCAINE 0.2 g/1 g
INACTIVE INGREDIENTS: FD&C BLUE NO. 1; D&C RED NO. 30; EUGENOL; ALUMINUM OXIDE; OXYQUINOLINE SULFATE; PETROLATUM; CARBOXYMETHYLCELLULOSE SODIUM, UNSPECIFIED FORM

Benzodent

ACTIVE INGREDIENT

Benzocaine 20%

PURPOSE

Pain reliever

INDICATIONS AND USAGE

For the temporary relief of pain due to minor irritation of the mouth and gums caused by dentures or orthodontic appliances or injury to mouth and gums.

DOSAGE AND ADMINISTRATION

Adults and children 12 years and over:

- remove cap, break metal seal with cap point
- apply directly to the gums or to the denture surface that comes in contact with the affected area of the gums
- if you are using the dentures, wait a few minutes then reinsert dentures and you may use your regular denture adhesive with this product
- use up to 4 times daily or as directed by a dentist or doctor
- children under 12 years of age should be supervised in the use of this product

children under 12 years: consult a dentist or doctor

WARNINGS

Methemoglobinemia warning: Use of this product may cause methemoglobinemia, a serious condition that must be treated promptly because it reduces the amount of oxygen carried to the blood. This can occur even if you have used this product before. Stop use and seek immedicate medical attention if you or a child in your care develops:

- pale, gray or blue colored skin (cyanosis)
- headache
- rapid heart rate
- shortness of breath
- dizziness or lightheadedness
- fatigue or lack of energy

Alllergy alert: Do not use if you have a history of allergy to local anetsthetics such as procaine, butacaine, benzocaine, or other "caine: anesthetics. Localized allergic reactions may occur after prolonged or repeated use.

Do not use

- for more than 7 consecutive days unless directed by a dentist of a doctor
- for teething
- in children under 2 years of age

When using this product

- avoid contact with eyes
- do not exceed recommended dosage

Stop use and ssk a doctor or dentist if

- sore mouth symptoms do not improve in 7 days
- swelling, rash or fever develops
- irritation, pain or redness persists or worsens

Keep out of reach of children.

In case of overdose, get medical help or contact a Poison Control Center right away. Quick medical attention is critical for adults as well as for children even if you do not notice any signs or symptoms.

INACTIVE INGREDIENT

cellulose gum, D&C red no.30 lake, eugneol, FD&C blue no. 1 lake, oxyquinoline sulfate, petrolatum